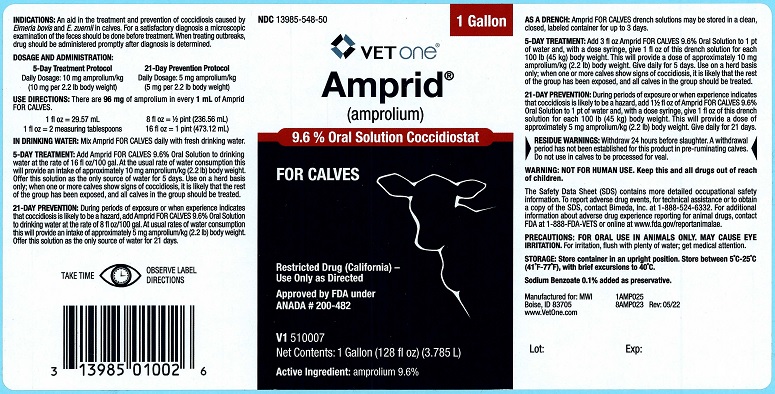 DRUG LABEL: Amprid FOR CALVES
NDC: 13985-548 | Form: SOLUTION
Manufacturer: MWI/VetOne
Category: animal | Type: OTC ANIMAL DRUG LABEL
Date: 20230111

ACTIVE INGREDIENTS: AMPROLIUM 96 mg/1 mL

DESCRIPTION

Amprid®

(amprolium)

9.6% Oral Solution Coccidiostat

FOR CALVES

Restricted Drug (California) – Use Only as Directed

Approved by FDA under ANADA # 200-482

Net Contents: 1Gallon (128 fl oz) (3.785 L)

Active Ingredient: amprolium 9.6%

INDICATIONS AND USAGE

INDICATIONS: An aid in the treatment and prevention of coccidiosis caused by Eimeria bovis and E. zuernii in calves. For a satisfactory diagnosis a microscopic examination of the feces should be done before treatment. When treating outbreaks, drug should be administered promptly after diagnosis is determined.

DOSAGE AND ADMINISTRATION:

USE DIRECTIONS: There are 96 mg of amprolium in every 1 mL of Amprid FOR CALVES

5 Day Treatment Protocol | 21 Day Prevention Protocol
Daily Dosage: 10 mg amprolium/kg; (10 mg per 2.2 lb body weight) | Daily Dosage: 5 mg amprolium/kg; (5 mg per 2.2 lb body weight)

USE DIRECTIONS: There are 96 mg of amprolium in every 1 mL of Amprid FOR CALVES.

1 fl oz = 29.57 mL

1 fl oz = 2 measuring tablespoons

8 fl oz = ½ pint (236.56 mL)

16 fl oz = 1 pint (473.12 mL)

IN DRINKING WATER: Mix Amprid FOR CALVES daily with fresh drinking water.

5-DAY TREATMENT: Add Amprid FOR CALVES 9.6% Oral Solution to drinking water at the rate of 16 fl oz/100 gal. At the usual rate of water consumption this will provide an intake of approximately 10 mg amprolium/kg (2.2 lb) body weight. Offer this solution as the only source of water for 5 days. Use on a herd basis only; when one or more calves show signs of coccidiosis, it is likely that the rest of the group has been exposed, and all calves in the group should be treated.

21-DAY PREVENTION: During periods of exposure or when experience indicates that coccidiosis is likely to be a hazard, add Amprid FOR CALVES 9.6% Oral Solution to drinking water at the rate of 8 fl oz/100 gal. At usual rates of water consumption, this will provide an intake of approximately 5 mg amprolium/kg (2.2 lb) body weight. Offer this solution as the only source of water for 21 days.

AS A DRENCH: Amprid FOR CALVES drench solutions may be stored in a clean, closed, labeled container for up to 3 days.

5-DAY TREATMENT: Add 3 fl oz Amprid FOR CALVES 9.6% Oral Solution to 1 pt of water and, with a dosage syringe, give 1 fl oz of this drench solution for each 100 lb (45 kg) body weight. This will provide a dose of approximately 10 mg amprolium/kg (2.2) body weight. Give daily for 5 days. Use on a herd basis only; when one or more calves show signs of coccidiosis, it is likely that the rest of the group has been exposed, and all calves should be treated.

21-DAY PREVENTION: During periods of exposure or when experience indicates that coccidiosis is likely to be a hazard, add 1 1/2 fl oz of Amprid FOR CALVES 9.6% Oral Solution to 1 pt of water and, with a dose syringe, give 1 fl oz of this solution for each 100 lb (45 kg) body weight. This will provide a dose of approximately 5 mg amprolium/kg (2.2 lb) body weight. Give daily for 21 days.

RESIDUE WARNING

RESIDUE WARNING: Withdraw 24 hours before slaughter. A withdrawal period has not been established for this product in pre-ruminating calves. Do not use in calves to be processed for veal.

WARNINGS

WARNING: NOT FOR HUMAN USE. Keep this and all drugs out of reach of children.

The Safety Data Sheet (SDS) contains more detailed occupational safety information. To report adverse drug events, for technical assistance or to obtain a copy of the SDS, contact Bimeda, Inc. at 1-888-524-6332. For additional information about adverse drug experience reporting for animal drugs, contact FDA at 1-888-FDA-VETS or online at www.fda.gov/reportanimalae.

PRECAUTIONS

PRECAUTIONS: FOR ORAL USE IN ANIMALS ONLY. MAY CAUSE EYE IRRITATION. For irritation, flush with plenty of water; get medical attention.

STORAGE AND HANDLING

STORAGE: Store container in an upright position. Store between 5°C - 25°C (41°F - 77°F), with brief excursions to 40°C.

Sodium Benzoate 0.1% added as preservative.